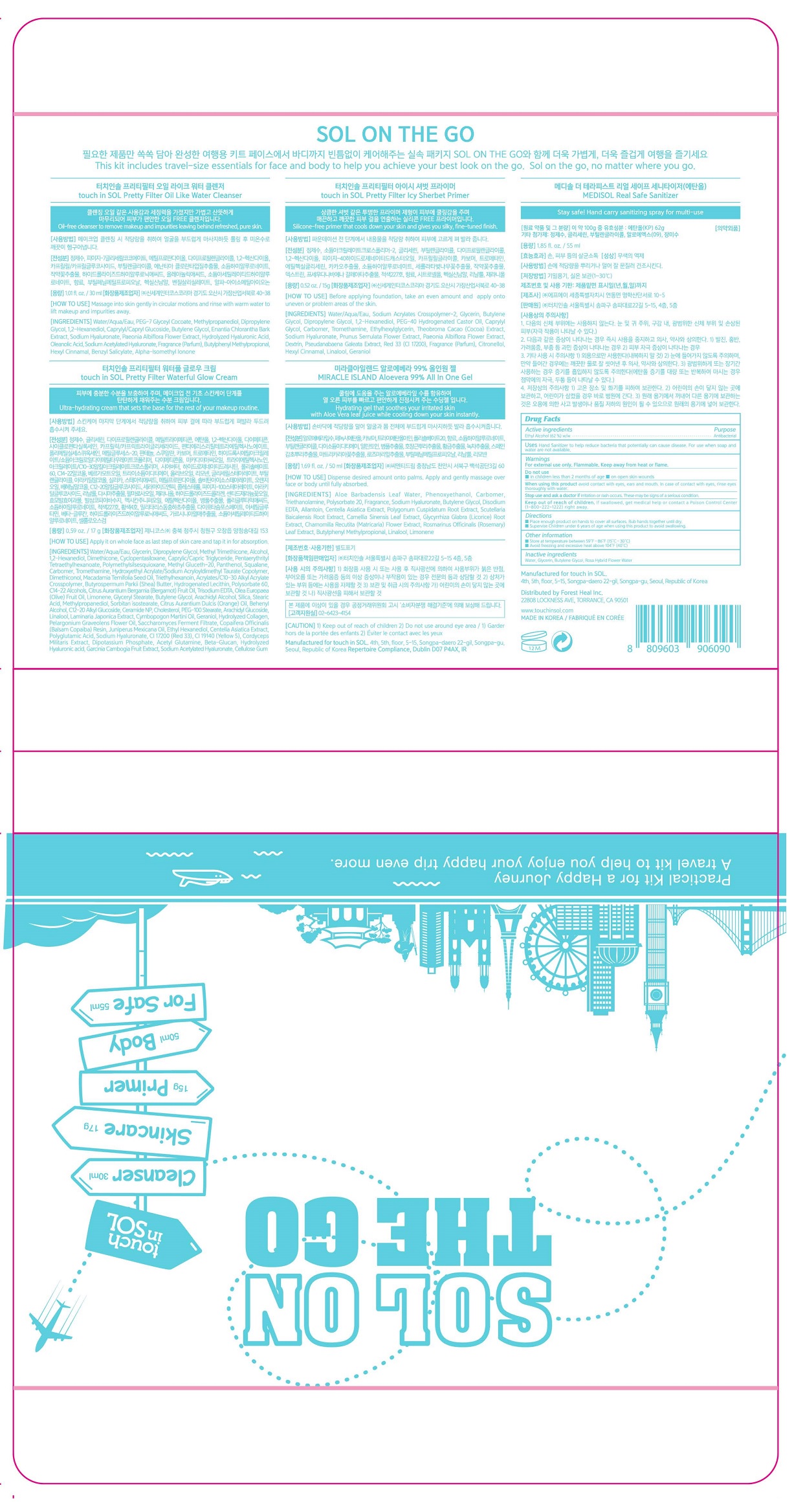 DRUG LABEL: SOL ON THE GO
NDC: 74813-103 | Form: LIQUID
Manufacturer: Forest Heal Inc.
Category: otc | Type: HUMAN OTC DRUG LABEL
Date: 20200910

ACTIVE INGREDIENTS: ALCOHOL 62 mL/100 mL
INACTIVE INGREDIENTS: BUTYLENE GLYCOL; GLYCERIN; WATER

SOL ON THE GO

Active ingredient

Ethanol 62%

Uses

Hand sanitizer to help reduce bacteria that potentially can cause disease. For use when soap and water are not available.

Purpose

Antibacterial

Warnings

For external use only. Flammable. Keep away from heat or flame.

Do not use

- in children less than 2 months of age
- on open skin wounds

When using this product

avoid contact with eyes, ears and mouth. In case of contact with eyes, rinse eyes thoroughly with water.

Stop use and ask a doctor if

irritation or rash occurs. These may be signs of a serious condition.

Keep out of reach of children. If swallowed, get medical help or contact a Poison Control Center (1-800-222-1222) right away.

Directions

- Place enough product on hands to cover all surfaces. Rub hands together until dry.
- Supervise Children under 6 years of age when using this product to avoid swallowing.

Inactive ingredients

Water, Glycerin, Butylene Glycol. Rosa Hybrid Flower Water

Keep out of reach of children. If swallowed, get medical help or contact a Poison Control Center (1-800-222-1222) right away.